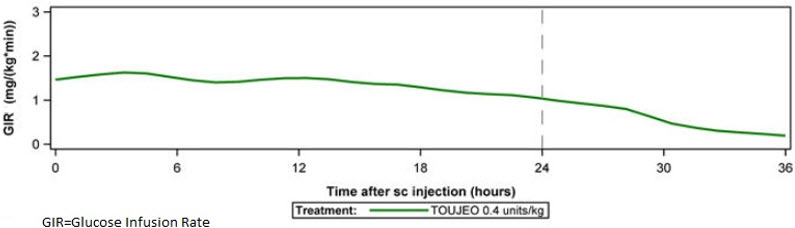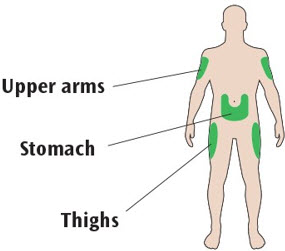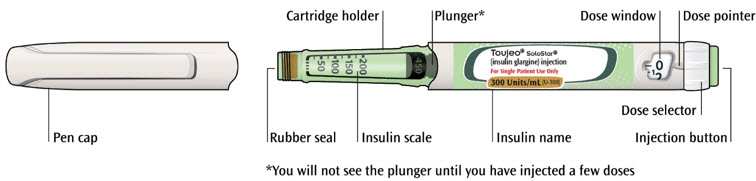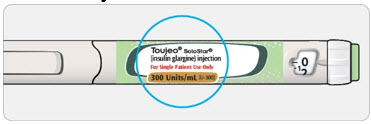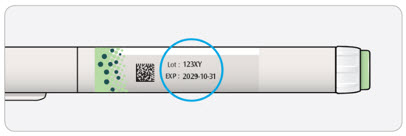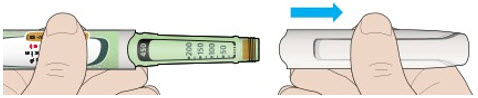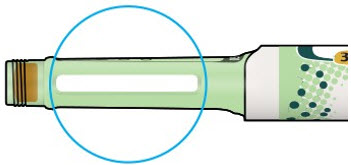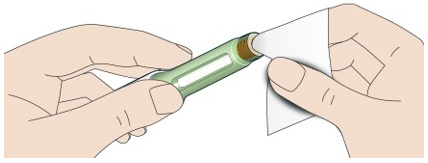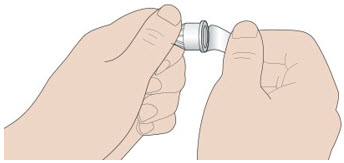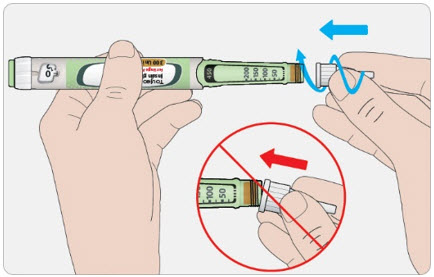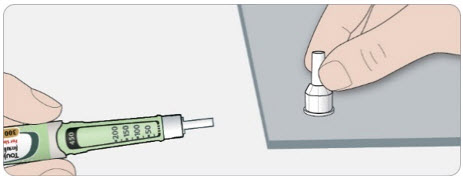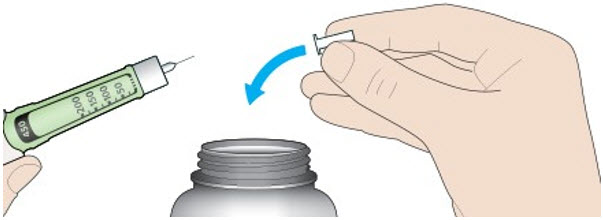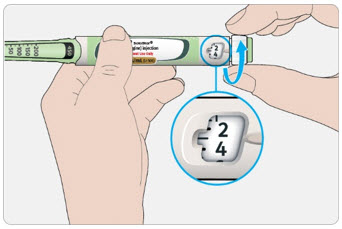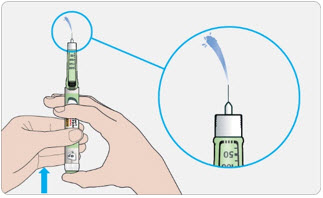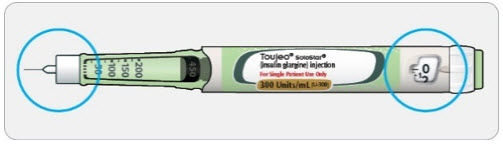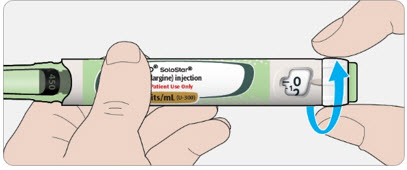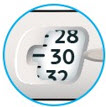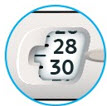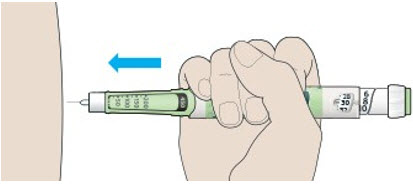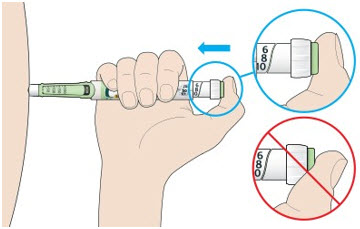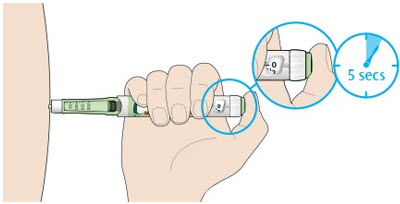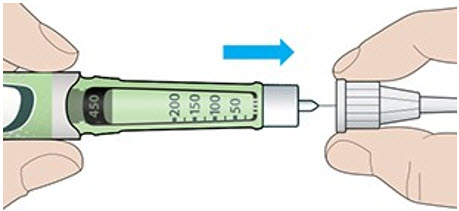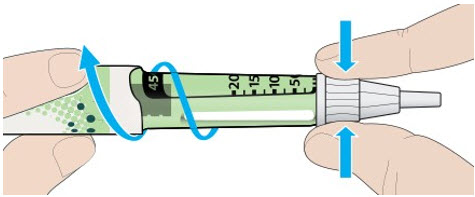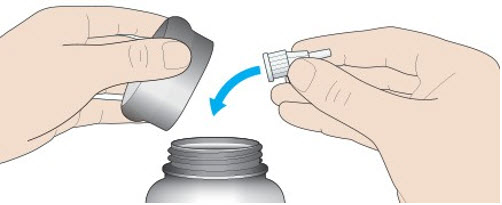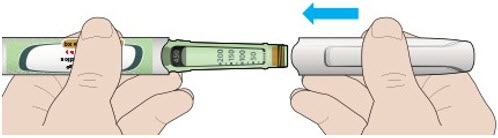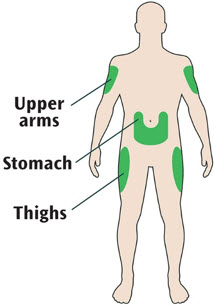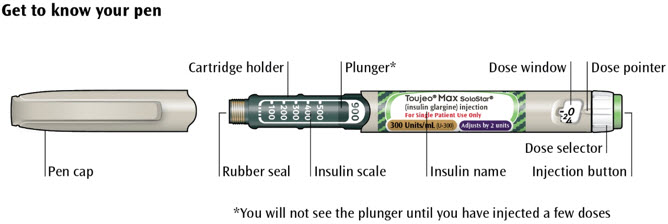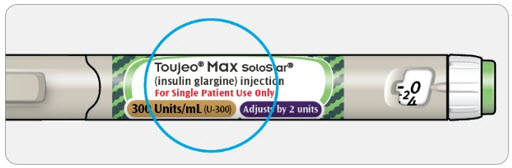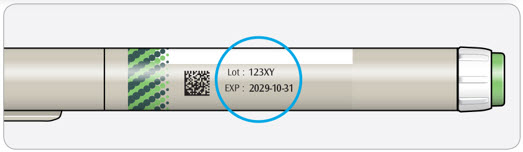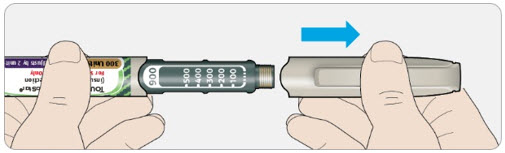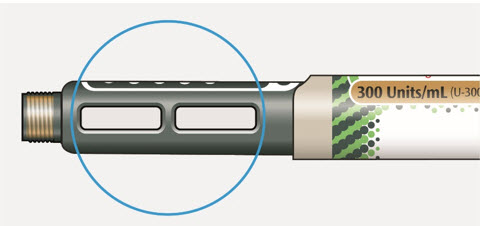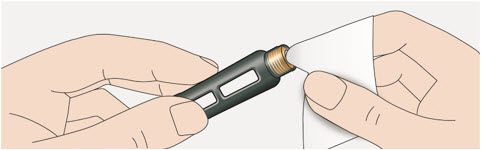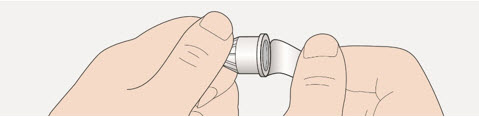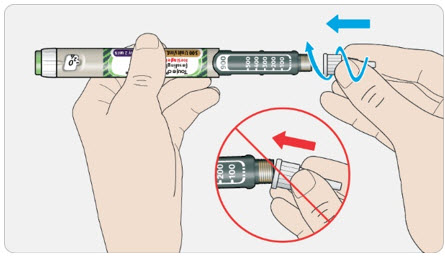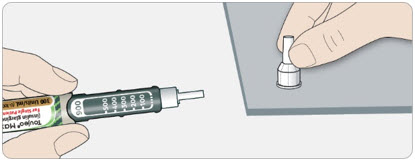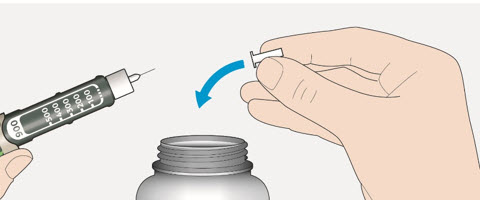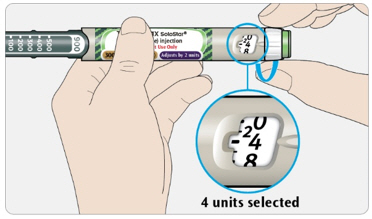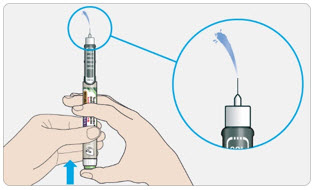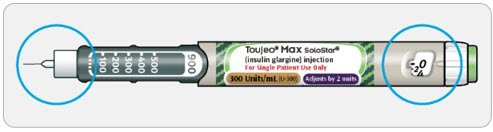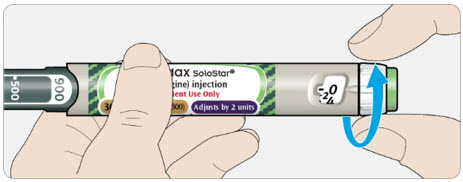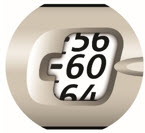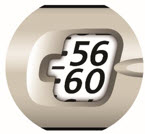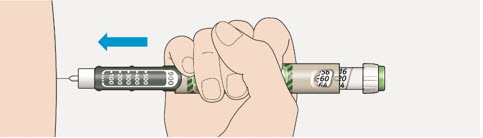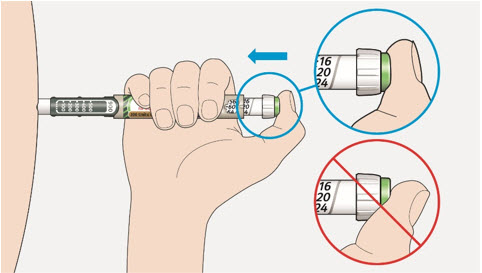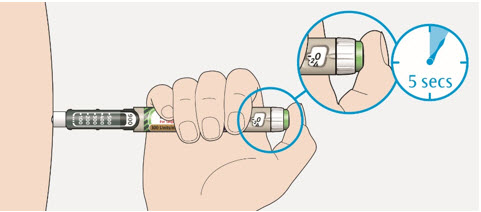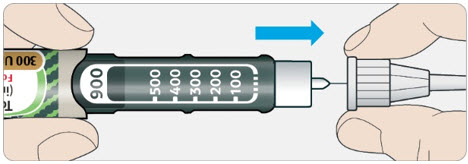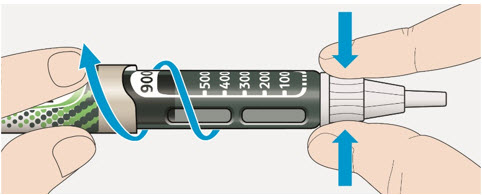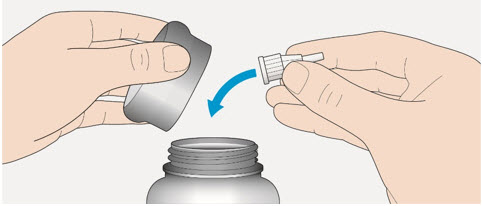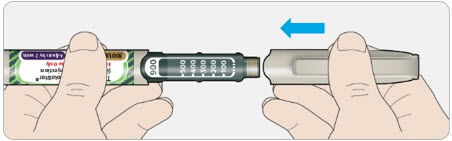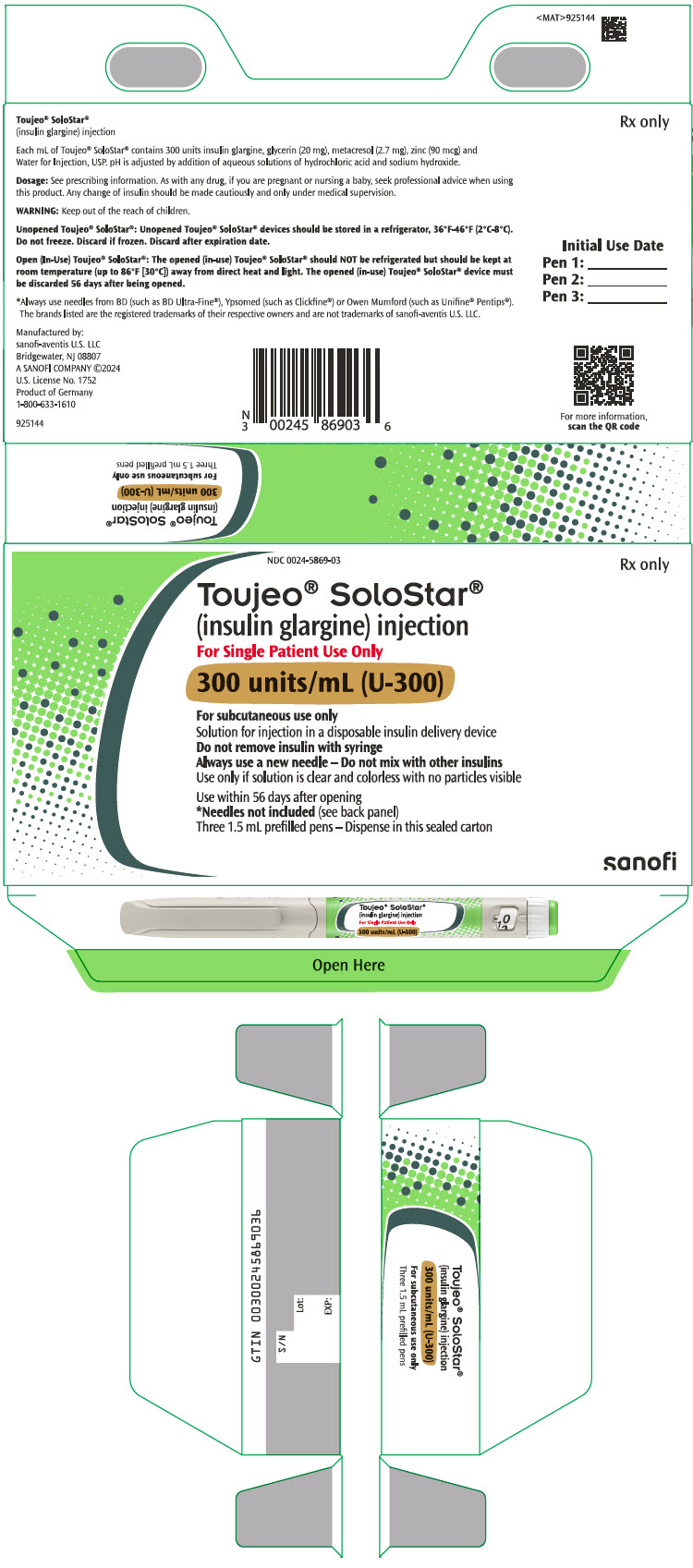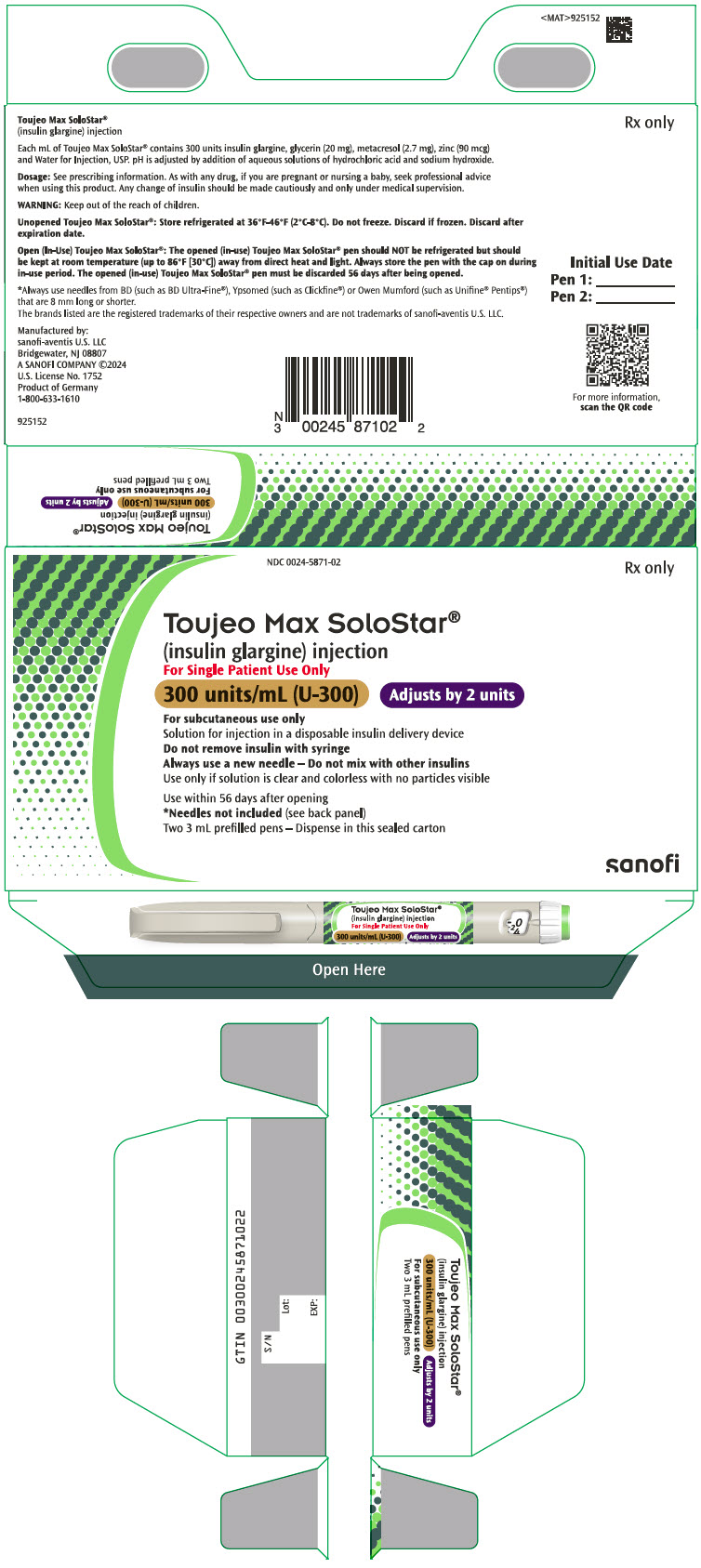 DRUG LABEL: TOUJEO
NDC: 0024-5869 | Form: INJECTION, SOLUTION
Manufacturer: Sanofi-Aventis U.S. LLC
Category: prescription | Type: HUMAN PRESCRIPTION DRUG LABEL
Date: 20250530

ACTIVE INGREDIENTS: insulin glargine 300 U/1 mL
INACTIVE INGREDIENTS: zinc 90 ug/1 mL; metacresol 2.7 mg/1 mL; glycerin 20 mg/1 mL; water

HIGHLIGHTS OF PRESCRIBING INFORMATION

These highlights do not include all the information needed to use TOUJEO® U-300 safely and effectively. See full prescribing information for TOUJEO® U-300.
TOUJEO U-300 (insulin glargine) injection, for subcutaneous use
Initial U.S. Approval: 2015

1 INDICATIONS AND USAGE

TOUJEO is a long-acting human insulin analog indicated to improve glycemic control in adults and pediatric patients 6 years and older with diabetes mellitus. (1)

Limitations of Use:

Not recommended for the treatment of diabetic ketoacidosis. (1)

2 DOSAGE AND ADMINISTRATION

- Individualize dose based on type of diabetes, metabolic needs, blood glucose monitoring results and glycemic control goal. (2.2)
- Administer subcutaneously into the abdominal area, thigh, or deltoid once daily at any time during the day, at the same time every day. (2.1)
- Rotate injection sites to reduce risk of lipodystrophy and localized cutaneous amyloidosis. (2.1)
- Do not dilute or mix with any other insulin or solution. (2.1)
- See Full Prescribing Information for the recommended starting dosage in patients with type 2 diabetes and how to switch to TOUJEO from other insulins (2.3, 2.4)
- Closely monitor glucose when switching to TOUJEO and during initial weeks thereafter. (2.4)

3 DOSAGE FORMS AND STRENGTHS

Injection: 300 units/mL (U-300) insulin glargine in:

- 1.5 mL SoloStar single-patient-use prefilled pen (3)
- 3 mL Max SoloStar single-patient-use prefilled pen (3)

4 CONTRAINDICATIONS

- During episodes of hypoglycemia (4)
- Hypersensitivity to insulin glargine or any excipients in TOUJEO (4)

5 WARNINGS AND PRECAUTIONS

- Never share a TOUJEO SoloStar or TOUJEO Max SoloStar single-patient-use prefilled pen between patients, even if the needle is changed. (5.1)
- Hyperglycemia or hypoglycemia with changes in insulin regimen: Make changes to a patient's insulin regimen (e.g., insulin strength, manufacturer, type, injection site, or method of administration) under close medical supervision with increased frequency of blood glucose monitoring. (5.2)
- Hypoglycemia: May be life-threatening. Increase frequency of glucose monitoring with changes to: insulin dosage, concomitant drugs, meal pattern, physical activity, and in patients with renal impairment or hepatic impairment or hypoglycemia unawareness. (5.3, 6.1)
- Hypoglycemia Due to Medication errors: Accidental mix-ups between insulin products can occur. Instruct patients to check insulin labels before injection. (5.4)
- Hypersensitivity reactions: Severe, life-threatening, generalized allergy, including anaphylaxis, can occur. Discontinue TOUJEO, monitor and treat if indicated. (5.5, 6.1)
- Hypokalemia: May be life-threatening. Monitor potassium levels in patients at risk of hypokalemia and treat if indicated. (5.6)
- Fluid retention and heart failure with concomitant use of Thiazolidinediones (TZDs): Observe for signs and symptoms of heart failure; consider dosage reduction or discontinuation if heart failure occurs. (5.7)

6 ADVERSE REACTIONS

Adverse reactions commonly associated with TOUJEO (≥5%) are:

- Hypoglycemia, allergic reactions, injection site reaction, lipodystrophy, pruritus, rash, edema, and weight gain. (6.1, 6.2)

To report SUSPECTED ADVERSE REACTIONS, contact sanofi-aventis at 1-800-633-1610 or FDA at 1-800-FDA-1088 or www.fda.gov/medwatch.

7 DRUG INTERACTIONS

- Drugs that Affect Glucose Metabolism: Adjustment of insulin dosage may be needed. (7)
- Antiadrenergic Drugs (e.g., beta-blockers, clonidine, guanethidine, and reserpine): Signs and symptoms of hypoglycemia may be reduced or absent. (5.3, 7)

FULL PRESCRIBING INFORMATION

1 INDICATIONS AND USAGE

TOUJEO is indicated to improve glycemic control in adults and pediatric patients 6 years of age and older with diabetes mellitus.

Limitations of Use:

TOUJEO is not recommended for the treatment of diabetic ketoacidosis.

2 DOSAGE AND ADMINISTRATION

2.1 Important Administration Instructions

- Always check insulin labels before administration [see Warnings and Precautions (5.4)].
- Visually inspect the TOUJEO solution for particulate matter and discoloration prior to administration and only use if the solution is clear and colorless with no visible particles.
- Inject TOUJEO subcutaneously into the abdominal area, thigh, or deltoid.
- Rotate injection sites within the same region from one injection to the next to reduce the risk of lipodystrophy and localized cutaneous amyloidosis. Do not inject into areas of lipodystrophy or localized cutaneous amyloidosis [see Warnings and Precautions (5.2), Adverse Reactions (6)].
- Use TOUJEO with caution in patients with visual impairment who may rely on audible clicks to dial their dose.
- Do not administer TOUJEO intravenously or in an insulin pump.
- Do not dilute or mix TOUJEO with any other insulin products or solutions.
- Never transfer TOUJEO from the cartridges of the TOUJEO SoloStar or TOUJEO Max SoloStar prefilled pen into a syringe for administration [see Warnings and Precautions (5.4)].

2.2 General Dosing Instructions

- TOUJEO is available in 2 single-patient-use prefilled pens:
  - The TOUJEO SoloStar prefilled pen contains 450 units of insulin glargine. It delivers doses in 1-unit increments and can deliver up to 80 units in a single injection.
  - The TOUJEO Max SoloStar prefilled pen contains 900 units of insulin glargine. It delivers doses in 2-unit increments and can deliver up to 160 units in a single injection. It is recommended for patients requiring at least 20 units per day.
- When changing between TOUJEO SoloStar and TOUJEO Max SoloStar, if the patient's previous dose was an odd number, the dose should be increased or decreased by 1 unit to match the dose increments dialable on each prefilled pen.
- The dose counter of the TOUJEO SoloStar or TOUJEO Max SoloStar prefilled pen shows the number of units of TOUJEO to be injected and no conversion is required.
- Inject TOUJEO subcutaneously once a day at the same time of day.
- During changes to a patient's insulin regimen, increase the frequency of blood glucose monitoring [see Warnings and Precautions (5.2)].
- Individualize and titrate the dosage of TOUJEO based on the patient's metabolic needs, blood glucose monitoring results, and glycemic control goal.
- Titrate the dose of TOUJEO no more frequently than every 3 to 4 days.
- Dosage adjustments may be needed with changes in physical activity, changes in meal patterns (i.e., macronutrient content or timing of food intake), changes in renal or hepatic function or during acute illness to minimize the risk of hypoglycemia or hyperglycemia [see Warnings and Precautions (5.2) and Use in Specific Populations (8.6, 8.7)].

2.3 Starting Dose in Insulin-Naive Pediatric and Adult Patients

Recommended Starting Dosage in Patients with Type 1 Diabetes

- The recommended starting dose of TOUJEO in insulin-naive patients with type 1 diabetes is approximately one-third to one-half of the total daily insulin dose. The remainder of the total daily insulin dose should be given as a short-acting insulin and divided between each daily meal. As a general rule, 0.2 to 0.4 units of insulin per kilogram of body weight can be used to calculate the initial total daily insulin dose in insulin-naive patients with type 1 diabetes.
- The maximum glucose lowering effect of a dose of TOUJEO may take five days to fully manifest and the first dose may be insufficient to cover metabolic needs in the first 24 hours of use [see Clinical Pharmacology (12.2)]. When initiating TOUJEO, monitor glucose daily.

Recommended Starting Dosage in Patients with Type 2 Diabetes

- The recommended starting dose of TOUJEO in insulin-naive patients with type 2 diabetes is 0.2 units per kilogram of body weight once daily.

2.4 Starting Dose in Pediatric and Adult Patients with Either Type 1 or Type 2 Diabetes Already on Insulin Therapy

Dosage adjustments are recommended to lower the risk of hypoglycemia when switching patients to TOUJEO from another insulin therapy [see Warnings and Precautions (5.3)].

- For patients currently on once-daily long or intermediate-acting insulin, start TOUJEO at the same unit dose as the once-daily long-acting insulin dose. For patients controlled on LANTUS (insulin glargine, 100 units/mL), expect that a higher daily dose of TOUJEO will be needed to maintain the same level of glycemic control [see Clinical Pharmacology (12.2) and Clinical Studies (14.1)].
- For patients currently on twice-daily long or intermediate-acting insulin, start TOUJEO at 80% of the total daily NPH or insulin detemir twice-daily dosage.
- When switching patients to TOUJEO, monitor glucose frequently in the first weeks of therapy [see Warnings and Precautions (5.2) and Clinical Pharmacology (12.2)].

3 DOSAGE FORMS AND STRENGTHS

Injection: 300 units/mL (U-300) of insulin glargine in a clear, colorless, solution available as:

- 1.5 mL SoloStar single-patient-use prefilled pen (450 units per 1.5 mL pen)
- 3 mL Max SoloStar single-patient-use prefilled pen (900 units per 3 mL pen)

4 CONTRAINDICATIONS

TOUJEO is contraindicated:

- During episodes of hypoglycemia [see Warnings and Precautions (5.3)].
- In patients with hypersensitivity to insulin glargine or any excipients in TOUJEO [see Warnings and Precautions (5.5)].

5 WARNINGS AND PRECAUTIONS

5.1 Never Share a TOUJEO SoloStar or TOUJEO Max SoloStar Pen Between Patients

TOUJEO SoloStar or TOUJEO Max SoloStar single-patient-use prefilled pens must never be shared between patients, even if the needle is changed. Pen sharing poses a risk for transmission of blood-borne pathogens.

5.2 Hyperglycemia or Hypoglycemia with Changes in Insulin Regimen

Changes in Insulin Regimen Including Changes to Administration Site

Changes in an insulin regimen (e.g., insulin strength, manufacturer, type, injection site, or method of administration) may affect glycemic control and predispose to hypoglycemia [see Warnings and Precautions (5.3)] or hyperglycemia. Repeated insulin injections into areas of lipodystrophy or localized cutaneous amyloidosis have been reported to result in hyperglycemia, and a sudden change in the injection site (to unaffected area) has been reported to result in hypoglycemia [see Adverse Reactions (6)].

Make any changes to a patient's insulin regimen under close medical supervision with increased frequency of blood glucose monitoring. Advise patients who have repeatedly injected into areas of lipodystrophy or localized cutaneous amyloidosis to change the injection site to unaffected areas and closely monitor for hypoglycemia. For patients with type 2 diabetes, dosage adjustments of concomitant oral antidiabetic products may be needed.

Changing to TOUJEO from other Insulin Therapies

On a unit-to-unit basis, TOUJEO has a lower glucose lowering effect than LANTUS [see Clinical Pharmacology (12.2)]. In clinical trials, patients who changed to TOUJEO from other basal insulins experienced higher average fasting plasma glucose levels in the first weeks of therapy compared to patients who were changed to LANTUS. Higher doses of TOUJEO were required to achieve similar levels of glucose control compared to LANTUS in clinical trials [see Clinical Studies (14.1)].

The onset of action of TOUJEO develops over 6 hours following an injection. In type 1 diabetes patients treated with IV insulin, consider the longer onset of action of TOUJEO before stopping IV insulin. The full glucose lowering effect may not be apparent for at least 5 days [see Dosage and Administration (2.2) and Clinical Pharmacology (12.2)].

To minimize the risk of hyperglycemia when initiating TOUJEO monitor glucose daily, titrate TOUJEO as described in this prescribing information, and adjust coadministered glucose-lowering therapies per standard of care [see Dosage and Administration (2.2, 2.3)].

5.3 Hypoglycemia

Hypoglycemia is the most common adverse reaction associated with insulin, including TOUJEO. Severe hypoglycemia can cause seizures, may be life-threatening, or cause death. Hypoglycemia can impair concentration ability and reaction time; this may place the patient and others at risk in situations where these abilities are important (e.g., driving, or operating other machinery). Hypoglycemia can happen suddenly, and symptoms may differ in each patient and change over time in the same patient. Symptomatic awareness of hypoglycemia may be less pronounced in patients with longstanding diabetes, in patients with diabetic neuropathy, in patients using drugs that block the sympathetic nervous system (e.g., beta-blockers) [see Drug Interactions (7)], or who experience recurrent hypoglycemia.

The long-acting effect of TOUJEO may delay recovery from hypoglycemia compared to shorter-acting insulins.

Risk Factors for Hypoglycemia

The timing of hypoglycemia usually reflects the time-action profile of the administered insulin formulation. As with all insulins, the glucose lowering effect time course of TOUJEO may vary in different patients or at different times in the same patient and depends on many conditions, including the area of injection as well as the injection site blood supply and temperature [see Clinical Pharmacology (12.2)]. Other factors which may increase the risk of hypoglycemia include changes in meal pattern (e.g., macronutrient content or timing of meals), changes in level of physical activity, or changes to concomitant drugs [see Drug Interactions (7)]. Patients with renal or hepatic impairment may be at higher risk of hypoglycemia [see Use in Specific Populations (8.6, 8.7)].

Risk Mitigation Strategies for Hypoglycemia

Patients and caregivers must be educated to recognize and manage hypoglycemia. Self-monitoring of blood glucose plays an essential role in the prevention and management of hypoglycemia. In patients at higher risk for hypoglycemia and patients who have reduced symptomatic awareness of hypoglycemia, increased frequency of blood glucose monitoring is recommended. To minimize the risk of hypoglycemia, do not administer TOUJEO intravenously, intramuscularly or in an insulin pump, or dilute or mix TOUJEO with any other insulin products or solutions.

5.4 Hypoglycemia Due to Medication Errors

Accidental mix-ups between insulin products have been reported. To avoid medication errors between TOUJEO and other insulins, instruct patients to always check the insulin label before each injection.

To avoid dosing errors and potential overdose, never use a syringe to remove TOUJEO from the TOUJEO SoloStar or TOUJEO Max SoloStar prefilled pen into a syringe [see Dosage and Administration (2.4) and Warnings and Precautions (5.3)].

5.5 Hypersensitivity Reactions

Severe, life-threatening, generalized allergy, including anaphylaxis, can occur with insulins, including TOUJEO. If hypersensitivity reactions occur, discontinue TOUJEO; treat per standard of care and monitor until symptoms and signs resolve [see Adverse Reactions (6)]. TOUJEO is contraindicated in patients who have had hypersensitivity reactions to insulin glargine or any of the excipients in TOUJEO.

5.6 Hypokalemia

All insulins, including TOUJEO, cause a shift in potassium from the extracellular to intracellular space, possibly leading to hypokalemia. Untreated hypokalemia may cause respiratory paralysis, ventricular arrhythmia, and death. Monitor potassium levels in patients at risk for hypokalemia, if indicated (e.g., patients using potassium-lowering medications, patients taking medications sensitive to serum potassium concentrations).

5.7 Fluid Retention and Heart Failure with Concomitant Use of PPAR-gamma Agonists

Thiazolidinediones (TZDs), which are peroxisome proliferator-activated receptor (PPAR)-gamma agonists, can cause dose-related fluid retention, when used in combination with insulin. Fluid retention may lead to or exacerbate heart failure. Patients treated with insulin, including TOUJEO, and a PPAR-gamma agonist should be observed for signs and symptoms of heart failure. If heart failure develops, it should be managed according to current standards of care, and discontinuation or dose reduction of the PPAR-gamma agonist must be considered.

6 ADVERSE REACTIONS

The following adverse reactions are discussed elsewhere:

- Hyperglycemia or Hypoglycemia with Changes in Insulin Regimen [see Warnings and Precautions (5.2)]
- Hypoglycemia [see Warnings and Precautions (5.3)]
- Hypoglycemia due to medication errors [see Warnings and Precautions (5.4)]
- Hypersensitivity Reactions [see Warnings and Precautions (5.5)]
- Hypokalemia [see Warnings and Precautions (5.6)]

6.1 Clinical Trials Experience

Because clinical trials are conducted under widely varying conditions, adverse reaction rates observed in the clinical trials of a drug cannot be directly compared to rates in the clinical trials of another drug and may not reflect the rates actually observed in clinical practice.

The data in Table 1 reflect the exposure of 304 patients with type 1 diabetes to TOUJEO with mean exposure duration of 23 weeks. The type 1 diabetes population had the following characteristics: Mean age was 46 years and mean duration of diabetes was 21 years. Fifty-five percent were male, 86% were White, 5% were Black or African American, and 5% were Hispanic or Latino. At baseline, the mean eGFR was 82 mL/min/1.73 m^2 and 35% of patients had eGFR ≥90 mL/min/1.73 m^2. The mean body mass index (BMI) was 28 kg/m^2. HbA1c at baseline was greater than or equal to 8% in 58% of patients.

The data in Table 2 reflect the exposure of 1242 patients with type 2 diabetes to TOUJEO with mean exposure duration of 25 weeks. The type 2 diabetes population had the following characteristics: Mean age was 59 years and mean duration of diabetes was 13 years. Fifty-three percent were male, 88% were White, 7% were Black or African American, and 17% were Hispanic or Latino. At baseline, mean eGFR was 79 mL/min/1.73 m^2 and 27% of patients had an eGFR ≥90 mL/min/1.73 m^2. The mean BMI was 35 kg/m^2. HbA1c at baseline was greater than or equal to 8% in 66% of patients.

TOUJEO was studied in 233 pediatric patients (6–17 years of age) with type 1 diabetes for a mean duration of 26 weeks [see Clinical Studies (14.1)].

Common adverse reactions (occurring ≥5%) in TOUJEO-treated subjects during clinical trials in adult patients with type 1 diabetes mellitus and type 2 diabetes mellitus are listed in Table 1 and Table 2, respectively. Common adverse reactions for TOUJEO-treated pediatric subjects with type 1 diabetes mellitus were similar to the adverse reactions listed in Table 1. Hypoglycemia is discussed in a dedicated subsection below.

Table 1: Adverse Reactions Occurring ≥5% in Two Pooled Clinical Trials of 26 Weeks and 16 Weeks Duration in Adults with Type 1 Diabetes
 | TOUJEO + Mealtime Insulin ["mealtime insulin" refers to insulin glulisine, insulin lispro, or insulin aspart.] , % (n=304)
Nasopharyngitis | 12.8
Upper respiratory tract infection | 9.5

Table 2: Adverse Reactions Occurring ≥5% in Three Pooled Clinical Trials of 26 Weeks Duration in Adults with Type 2 Diabetes
 | TOUJEO [one of the trials in type 2 diabetes included mealtime insulin.] , % (n=1242)
Nasopharyngitis | 7.1
Upper respiratory tract infection | 5.7

Hypoglycemia

Hypoglycemia is the most commonly observed adverse reaction in patients treated with TOUJEO. The rates of reported hypoglycemia depend on the definition of hypoglycemia used, diabetes type, insulin dose, intensity of glucose control, background therapies, and other intrinsic and extrinsic patient factors. For these reasons, comparing rates of hypoglycemia in clinical trials for TOUJEO with the incidence of hypoglycemia for other products may be misleading and also may not be representative of hypoglycemia rates that will occur in clinical practice.

In the TOUJEO adult program, severe hypoglycemia was defined as an event requiring assistance of another person to administer a resuscitative action. In the pediatric program, severe hypoglycemia was defined as an event with semiconsciousness, unconsciousness, coma and/or convulsions in a patient who had altered mental status and could not assist in his own care, and who may have required glucagon or intravenous glucose.

The incidence of severe hypoglycemia in adult patients with type 1 diabetes receiving TOUJEO as part of a multiple daily injection regimen was 6.6% at 26 weeks. The incidence of hypoglycemia with a glucose level less than 54 mg/dL with or without symptoms was 77.7% at 26 weeks.

The incidence of severe hypoglycemia in pediatric patients with type 1 diabetes receiving TOUJEO as part of a multiple daily injection regimen was 6% at 26 weeks and the incidence of hypoglycemia accompanied by a self-monitored or plasma glucose value less than 54 mg/dL regardless of symptoms was 80.3%.

The incidence of severe hypoglycemia in adult patients with type 2 diabetes was 5% at 26 weeks in patients receiving TOUJEO as part of a multiple daily injection regimen, and 1.0% and 0.9% respectively at 26 weeks in the two studies where patients received TOUJEO as part of a basal-insulin only regimen. The incidence of hypoglycemia accompanied by a self-monitored or plasma glucose value less than 54 mg/dL regardless of symptoms in patients with type 2 diabetes receiving TOUJEO ranged from 9% to 44.6% at 26 weeks and the highest risk was again seen in patients receiving TOUJEO as part of a multiple daily injection regimen.

Insulin Initiation and Intensification of Glucose Control

Intensification or rapid improvement in glucose control has been associated with a transitory, reversible ophthalmologic refraction disorder, worsening of diabetic retinopathy, and acute painful peripheral neuropathy. However, long-term glycemic control decreases the risk of diabetic retinopathy and neuropathy.

Peripheral Edema

Insulin, including TOUJEO, may cause sodium retention and edema, particularly if previously poor metabolic control was improved by intensified insulin therapy.

Lipodystrophy

Long-term use of insulin, including TOUJEO, can cause lipoatrophy (depression in the skin) or lipohypertrophy (enlargement or thickening of tissue) in some patients and may affect insulin absorption [see Dosage and Administration (2.1)].

Weight Gain

Weight gain has occurred with insulins, including TOUJEO and has been attributed to the anabolic effects of insulin and the decrease in glucosuria.

Hypersensitivity Reactions

Patients taking TOUJEO experienced erythema, local edema, and pruritus at the site of injection. These conditions were usually self-limiting.

Severe cases of generalized allergy (anaphylaxis) have been reported.

6.2 Immunogenicity

As with all therapeutic proteins, there is potential for immunogenicity.

In a 6-month study of type 1 diabetes patients, 79% of patients who received TOUJEO once daily were positive for anti-insulin antibodies (AIA) at least once during the study, including 62% that were positive at baseline and 44% of patients who developed antidrug antibody (i.e., anti-insulin glargine antibody [ADA]) during the study. Eighty percent of the AIA-positive patients on TOUJEO with antibody test at baseline remained AIA positive at month 6.

In two 6-month studies in type 2 diabetes patients, 25% of patients who received TOUJEO once daily were positive for AIA at least once during the study, including 42% who were positive at baseline and 20% of patients who developed ADA during the study. Ninety percent of the AIA-positive patients on TOUJEO with antibody test at baseline, remained AIA positive at month 6.

The detection of antibody formation is highly dependent on the sensitivity and specificity of the assay and may be influenced by several factors such as: assay methodology, sample handling, timing of sample collection, concomitant medication, and underlying disease. For these reasons, comparison of the incidence of antibodies to TOUJEO with the incidence of antibodies in other studies or to other products may be misleading.

6.3 Postmarketing Experience

The following additional adverse reactions have been identified during postapproval use of TOUJEO. Because these reactions are reported voluntarily from a population of uncertain size, it is not always possible to reliably estimate their frequency or establish a causal relationship to drug exposure.

Localized cutaneous amyloidosis at the injection site has occurred. Hyperglycemia has been reported with repeated insulin injections into areas of localized cutaneous amyloidosis; hypoglycemia has been reported with a sudden change to an unaffected injection site.

7 DRUG INTERACTIONS

Table 3 includes clinically significant drug interactions with TOUJEO.

Table 3: Clinically Significant Drug Interactions with TOUJEO
Drugs That May Increase the Risk of Hypoglycemia
Drugs: | Antidiabetic agents, ACE inhibitors, angiotensin II receptor blocking agents, disopyramide, fibrates, fluoxetine, monoamine oxidase inhibitors, pentoxifylline, pramlintide, salicylates, somatostatin analogs (e.g., octreotide), and sulfonamide antibiotics, GLP-1 receptor agonists, DPP-4 inhibitors, and SGLT-2 inhibitors.
Intervention: | Dosage reductions and increased frequency of glucose monitoring may be required when TOUJEO is coadministered with these drugs.
Drugs That May Decrease the Blood Glucose Lowering Effect of TOUJEO
Drugs: | Atypical antipsychotics (e.g., olanzapine and clozapine), corticosteroids, danazol, diuretics, estrogens, glucagon, isoniazid, niacin, oral contraceptives, phenothiazines, progestogens (e.g., in oral contraceptives), protease inhibitors, somatropin, sympathomimetic agents (e.g., albuterol, epinephrine, terbutaline), and thyroid hormones.
Intervention: | Dosage increases and increased frequency of glucose monitoring may be required when TOUJEO is coadministered with these drugs.
Drugs That May Increase or Decrease the Blood Glucose Lowering Effect of TOUJEO
Drugs: | Alcohol, beta-blockers, clonidine, and lithium salts. Pentamidine may cause hypoglycemia, which may sometimes be followed by hyperglycemia.
Intervention: | Dosage adjustment and increased frequency of glucose monitoring may be required when TOUJEO is coadministered with these drugs.
Drugs That May Blunt Signs and Symptoms of Hypoglycemia
Drugs: | Beta-blockers, clonidine, guanethidine, and reserpine.
Intervention: | Increased frequency of glucose monitoring may be required when TOUJEO is coadministered with these drugs.

8 USE IN SPECIFIC POPULATIONS

8.1 Pregnancy

Risk Summary

Published studies with use of insulin glargine during pregnancy have not reported a clear association with insulin glargine and adverse developmental outcomes (see Data). There are risks to the mother and fetus associated with poorly controlled diabetes in pregnancy (see Clinical Considerations).

Rats and rabbits were exposed to insulin glargine in animal reproduction studies during organogenesis, respectively 50 times and 10 times the human subcutaneous dose of 0.2 unit/kg/day. Overall, the effects of insulin glargine did not generally differ from those observed with regular human insulin (see Data).

In the U.S. general population, the estimated background risk of major birth defects and miscarriage in clinically recognized pregnancies is 2% to 4% and 15% to 20%, respectively. The estimated background risk of major birth defects is 6% to 10% in women with pregestational diabetes with a peri-conceptional HbA1c >7 and has been reported to be as high as 20% to 25% in women with a peri-conceptional HbA1c >10. The estimated background risk of miscarriage for the indicated population is unknown.

Clinical Considerations

Disease-Associated Maternal and/or Embryo/fetal Risk

Hypoglycemia and hyperglycemia occur more frequently during pregnancy in patients with pre-gestational diabetes. Poorly controlled diabetes in pregnancy increases the maternal risk for diabetic ketoacidosis, preeclampsia, spontaneous abortions, preterm delivery, and delivery complications. Poorly controlled diabetes increases the fetal risk for major birth defects, stillbirth, and macrosomia-related morbidity.

Data

Human Data

Published data do not report a clear association with insulin glargine and major birth defects, miscarriage, or adverse maternal or fetal outcomes when insulin glargine is used during pregnancy. However, these studies cannot definitely establish the absence of any risk because of methodological limitations including small sample size and some lacking comparator groups.

Animal Data

Subcutaneous reproduction and teratology studies have been performed with insulin glargine and regular human insulin in rats and Himalayan rabbits. Insulin glargine was given to female rats before mating, during mating, and throughout pregnancy at doses up to 0.36 mg/kg/day, which is approximately 50 times the recommended human subcutaneous starting dosage of 0.2 Units/kg/day (0.007 mg/kg/day). In rabbits, doses of 0.072 mg/kg/day, which is approximately 10 times the recommended human subcutaneous starting dosage of 0.2 Units/kg/day (0.007 mg/kg/day), were administered during organogenesis. The effects of insulin glargine did not generally differ from those observed with regular human insulin in rats or rabbits. However, in rabbits, five fetuses from two litters of the high-dose group exhibited dilation of the cerebral ventricles. Fertility and early embryonic development appeared normal.

8.2 Lactation

Risk Summary

There are either no or only limited data on the presence of insulin glargine in human milk, the effects on breastfed infant, or the effects on milk production. Endogenous insulin is present in human milk. The developmental and health benefits of breastfeeding should be considered along with the mother's clinical need for TOUJEO, and any potential adverse effects on the breastfed child from TOUJEO or from the underlying maternal condition.

8.4 Pediatric Use

The safety and effectiveness of TOUJEO to improve glycemic control in pediatric patients 6 years of age and older with diabetes mellitus have been established.

The use of TOUJEO for this indication is supported by evidence from an adequate and well-controlled study in 463 pediatric patients 6 to 17 years of age with type 1 diabetes mellitus [see Clinical Studies (14.2)] and from studies in adults with diabetes mellitus [see Clinical Pharmacology (12.3), Clinical Studies (14.3)].

The safety and effectiveness of TOUJEO have not been established in pediatric patients less than 6 years of age.

8.5 Geriatric Use

In controlled clinical studies, 30 of 304 (9.8%) TOUJEO-treated patients with type 1 diabetes and 327 of 1242 (26.3%) TOUJEO-treated patients with type 2 diabetes were ≥65 years of age, among them 2.0% of the patients with type 1 and 3.0% of the patients with type 2 diabetes were ≥75 years of age. No overall differences in safety or effectiveness of TOUJEO have been observed between patients 65 years of age and older and younger adult patients.

Nevertheless, caution should be exercised when TOUJEO is administered to geriatric patients. In geriatric patients with diabetes, the initial dosing, dose increments, and maintenance dosage should be conservative to avoid hypoglycemia [see Warnings and Precautions (5.3), Adverse Reactions (6), and Clinical Studies (14)].

8.6 Renal Impairment

The effect of kidney impairment on the pharmacokinetics of TOUJEO has not been studied. Some studies with human insulin have shown increased circulating levels of insulin in patients with kidney failure. Frequent glucose monitoring and dose adjustment may be necessary for TOUJEO in patients with kidney impairment [see Warnings and Precautions (5.3)].

8.7 Hepatic Impairment

The effect of hepatic impairment on the pharmacokinetics of TOUJEO has not been studied. Frequent glucose monitoring and dose adjustment may be necessary for TOUJEO in patients with hepatic impairment [see Warnings and Precautions (5.3)].

10 OVERDOSAGE

Excess insulin administration may cause hypoglycemia and hypokalemia [see Warnings and Precautions (5.3, 5.6)]. Mild episodes of hypoglycemia can be treated with oral glucose. Lowering the insulin dosage, and adjustments in meal patterns, or physical activity level may be needed. More severe episodes of hypoglycemia with coma, seizure, or neurologic impairment may be treated with glucagon for emergency use or concentrated intravenous glucose. Sustained carbohydrate intake and observation may be necessary because hypoglycemia may recur after apparent clinical recovery. Hypokalemia must be corrected appropriately.

11 DESCRIPTION

Insulin glargine is a long-acting human insulin analog produced by recombinant DNA technology utilizing a nonpathogenic laboratory strain of Escherichia coli (K12) as the production organism. Insulin glargine differs from human insulin in that the amino acid asparagine at position A21 is replaced by glycine and two arginines remain at the C-terminus of the B-chain. Insulin glargine has a molecular weight of 6063 Da.

TOUJEO (insulin glargine) injection is a sterile, clear and colorless solution for subcutaneous injection. Each mL of TOUJEO contains 300 units of insulin glargine dissolved in a clear aqueous fluid.

The 1.5 mL TOUJEO SoloStar prefilled pen presentation contains the following inactive ingredients per mL: glycerin (20 mg), metacresol (2.7 mg), zinc (90 mcg), and Water for Injection, USP.

The 3 mL TOUJEO Max SoloStar prefilled pen presentation contains the following inactive ingredients per mL: glycerin (20 mg), metacresol (2.7 mg), zinc (90 mcg), and Water for Injection, USP.

The pH is adjusted by addition of aqueous solutions of hydrochloric acid and sodium hydroxide. TOUJEO has a pH of approximately 4.

12 CLINICAL PHARMACOLOGY

12.1 Mechanism of Action

The primary activity of insulin, including insulin glargine, is regulation of glucose metabolism. Insulin and its analogs lower blood glucose by stimulating peripheral glucose uptake, especially by skeletal muscle and fat, and by inhibiting hepatic glucose production. Insulin inhibits lipolysis and proteolysis and enhances protein synthesis.

12.2 Pharmacodynamics

Onset of Action

The pharmacodynamic profiles for TOUJEO given subcutaneously as a single dose of 0.4, 0.6, or 0.9 U/kg in a euglycemic clamp study in patients with type 1 diabetes showed that on average, the onset of action develops over 6 hours post dose for all three single doses of TOUJEO.

Single-Dose Pharmacodynamics

The pharmacodynamics for single 0.4, 0.6, and 0.9 U/kg doses of TOUJEO in 24 patients with type 1 diabetes mellitus was evaluated in a euglycemic clamp study. On a unit-to-unit basis, TOUJEO had a lower maximum (GIRmax) and 24-hour glucose lowering effect (GIR-AUC0–24) compared to LANTUS. The overall glucose lowering effect of TOUJEO 0.4 U/kg was 12% of the glucose lowering effect of an equivalent dose of LANTUS. Glucose lowering at least 30% of the effect of a single 0.4 U/kg dose of LANTUS was not observed until the single dose of TOUJEO exceeded 0.6 U/kg.

Multiple Once-Daily Dose Pharmacodynamics

The pharmacodynamics of TOUJEO after 8 days of daily injection was evaluated in 30 patients with type 1 diabetes. At steady state, the 24-hour glucose lowering effect (GIR-AUC0–24) of TOUJEO 0.4 U/kg was approximately 27% lower with a different distribution profile than that of an equivalent dose of LANTUS [see Dosage and Administration (2), Warnings and Precautions (5.2), and Clinical Pharmacology (12.3)]. The glucose lowering effect of a TOUJEO dose increased with each daily administration.

The pharmacodynamic profile for TOUJEO given subcutaneously as multiple once-daily subcutaneous injections of 0.4 U/kg in a euglycemic clamp study in patients with type 1 diabetes is shown in Figure 1.

Figure 1: Glucose Infusion Rate in Patients with Type 1 Diabetes in Multiple-Dose Administration of TOUJEO

Glucose infusion rate: determined as amount of glucose infused to maintain constant plasma glucose levels.

12.3 Pharmacokinetics

Absorption

The pharmacokinetic profiles for single 0.4, 0.6, and 0.9 U/kg doses of TOUJEO in 24 patients with type 1 diabetes mellitus was evaluated in a euglycemic clamp study. The median time to maximum serum insulin concentration was 12 (8–14), 12 (12–18), and 16 (12–20) hours, respectively. Mean serum insulin concentrations declined to the lower limit of quantitation of 5.02 µU/mL by 16, 28, and beyond 36 hours, respectively.

Steady-state insulin concentrations are reached by at least 5 days of once-daily subcutaneous administration of 0.4 U/kg to 0.6 U/kg doses of TOUJEO over 8 days in patients with type 1 diabetes mellitus.

After subcutaneous injection of TOUJEO, the intra-subject variability, defined as the coefficient of variation for the insulin exposure during 24 hours, was 21.0% at steady state.

Elimination

After subcutaneous injection of TOUJEO in diabetic patients, insulin glargine is metabolized at the carboxyl terminus of the B-chain with formation of two active metabolites M1 (21A-Gly-insulin) and M2 (21A-Gly-des-30B-Thr-insulin). The in vitro activity of M1 and M2 were similar to that of human insulin.

Specific Populations

Pediatrics

Population pharmacokinetic analysis was conducted for TOUJEO based on concentration data of its main metabolite M1 using data from 75 pediatric patients (6 to <18 years of age) with type 1 diabetes. The findings with regard to the effect of body weight on systemic exposure of M1 are generally consistent with findings in adults.

Elderly, Race, Sex, and Obesity

Effect of age ≥65, race, and sex on the pharmacokinetics of TOUJEO has not been evaluated. When weight is taken into account as a covariate on clearance, BMI is not an additional covariate.

13 NONCLINICAL TOXICOLOGY

13.1 Carcinogenesis, Mutagenesis, Impairment of Fertility

In mice and rats, standard two-year carcinogenicity studies with insulin glargine were performed at doses up to 0.455 mg/kg, which was for the rat approximately 65 times the recommended human subcutaneous starting dosage of 0.2 Units/kg/day (0.007 mg/kg/day). The findings in female mice were not conclusive due to excessive mortality in all dose groups during the study. Histiocytomas were found at injection sites in male rats (statistically significant) and male mice (not statistically significant) in acid vehicle containing groups. These tumors were not found in female animals, in saline control, or insulin comparator groups using a different vehicle. The relevance of these findings to humans is unknown.

Insulin glargine was not mutagenic in tests for detection of gene mutations in bacteria and mammalian cells (Ames and HGPRT test) and in tests for detection of chromosomal aberrations (cytogenetics in vitro in V79 cells and in vivo in Chinese hamsters).

In a combined fertility and prenatal and postnatal study in male and female rats at subcutaneous doses up to 0.36 mg/kg/day, which was approximately 50 times the recommended human subcutaneous starting dose of 0.2 Units/kg/day (0.007 mg/kg/day), maternal toxicity due to dose-dependent hypoglycemia, including some deaths, was observed. Consequently, a reduction of the rearing rate occurred in the high-dose group only. Similar effects were observed with NPH insulin.

14 CLINICAL STUDIES

14.1 Overview of Clinical Studies

The efficacy of TOUJEO given once daily was compared to that of once-daily LANTUS in 26-week, open-label, randomized, active-control, parallel studies of 546 adult patients and 463 pediatric patients with type 1 diabetes mellitus and 2,474 patients with type 2 diabetes mellitus (Tables 4 and 5). At trial end, the reduction in glycated hemoglobin (HbA1c) and fasting plasma glucose with TOUJEO titrated to goal was similar to that with LANTUS titrated to goal. At the end of the trial, depending on the patient population and concomitant therapy, patients were receiving a higher dose of TOUJEO than LANTUS.

14.2 Clinical Study in Adult and Pediatric Patients with Type 1 Diabetes

Adult Patients with Type 1 Diabetes

In an open-label, controlled study (Study A), patients with type 1 diabetes (n=546), were randomized to basal-bolus treatment with TOUJEO or LANTUS and treated for 26 weeks. TOUJEO and LANTUS were administered once daily in the morning (time period covering from pre-breakfast until pre-lunch) or in the evening (time period defined as prior to the evening meal until at bedtime). A mealtime insulin analogue was administered before each meal. Mean age was 47 years and mean duration of diabetes was 21 years. Fifty-seven percent were male, 85% were White, 5% Black or African American, and 5% were Hispanic or Latino; 32% of patients had GFR >90 mL/min/1.73 m^2. The mean BMI was approximately 27.6 kg/m^2. At week 26, treatment with TOUJEO provided a mean reduction in HbA1c that met the prespecified noninferiority margin of 0.4% (Table 4). Patients treated with TOUJEO used 18% more basal insulin than patients treated with LANTUS. There were no clinically important differences in glycemic control when TOUJEO was administered once daily in the morning or in the evening. There were no clinically important differences in body weight between treatment groups.

Table 4 : Type 1 Diabetes Mellitus – Adult Patients (TOUJEO plus mealtime insulin versus LANTUS plus mealtime insulin)
 | TOUJEO + Mealtime Insulin ["mealtime insulin" refers to insulin glulisine, insulin lispro or insulin aspart.] | LANTUS + Mealtime Insulin
Treatment duration | 26 weeks
Treatment in combination with | Fast-acting insulin analogue
Number of subjects treated (mITT [mITT: Modified intention-to-treat population.]) | 273 | 273
HbA1c (%)
Baseline mean | 8.13 | 8.12
Adjusted mean change from baseline | -0.40 | -0.44
Adjusted mean difference [Treatment difference: TOUJEO – LANTUS.] [95% Confidence Interval] | 0.04 [-0.10 to 0.18]
Fasting Plasma Glucose mg/dL
Baseline mean | 186 | 199
Adjusted mean change from baseline | -17 | -20
Adjusted mean difference [95% Confidence Interval] | 3 [-10 to 16]

Pediatric Patients with Type 1 Diabetes

The efficacy of TOUJEO was evaluated in a 26-week, randomized, open-label, multicenter trial (Study B) in 463 pediatric patients with type 1 diabetes mellitus. Patients were randomized to basal-bolus treatment with TOUJEO or LANTUS and treated for 26 weeks. TOUJEO and LANTUS were administered once daily in the morning or in the evening. A mealtime insulin analogue was administered before each meal.

The mean age of the trial population was 13 years; 31% were <12 years of age, 69% were ages ≥12 years of age. The mean duration of diabetes was 6 years. Of the 463 pediatric patients, 51% were male, 92% were White, 3% were Black or African American, and 30% were Hispanic or Latino. The mean baseline BMI percentile was 68.32.

At week 26, the difference in HbA1c reduction from baseline between TOUJEO and LANTUS was 0.02% with a 95% confidence interval (-0.16%; 0.20%) and met the prespecified noninferiority margin (0.3%). The results are presented in Table 5.

Table 5: Type 1 Diabetes Mellitus – Pediatric Patients at 26 weeks (TOUJEO plus mealtime insulin versus LANTUS plus mealtime insulin)
 | TOUJEO + Mealtime Insulin ["mealtime insulin" refers to insulin glulisine, insulin lispro or insulin aspart.] | LANTUS + Mealtime Insulin
Number of subjects (ITT [ITT: Intention-to-treat: all randomized subjects.]) | 233 | 230
HbA1c (%) [At week 26, change in HbA1c was missing for 3.9% and 4.3% of subjects, and change in FPG was missing for 12.4% and 12.2% of subjects, in TOUJEO and LANTUS respectively. Missing values were imputed with return-to-baseline method for subjects who permanently discontinued the treatment.]
Baseline mean | 8.65 | 8.61
Adjusted Mean change from baseline | -0.386 | -0.404
Adjusted Mean difference [Treatment difference: TOUJEO – LANTUS.] [95% Confidence Interval] | 0.018 [-0.159, 0.195]
Fasting Plasma Glucose (mg/dL)
Baseline mean | 202.70 | 204.51
Adjusted Mean change from baseline | -10.447 | -10.633
Adjusted Mean difference [95% Confidence Interval] | 0.185 [-18.131, 18.501]

14.3 Clinical Studies in Adult Patients with Type 2 Diabetes

In a 26-week open-label, controlled study (Study C, n=804), adults with type 2 diabetes were randomized to once-daily treatment in the evening with either TOUJEO or LANTUS. Short-acting mealtime insulin analogues with or without metformin were also administered. The average age was 60 years. The majority of patients were White (92%) and 53% were male; 20% of patients had GFR >90 mL/min/1.73 m^2. The mean BMI was approximately 36.6 kg/m^2. At week 26, treatment with TOUJEO provided a mean reduction in HbA1c that met the prespecified noninferiority margin of 0.4% compared to LANTUS (Table 6). Patients treated with TOUJEO used 11% more basal insulin than patients treated with LANTUS. There were no clinically important differences in body weight between treatment groups.

In two open-label, controlled studies (n=1670), adults with type 2 diabetes mellitus were randomized to either TOUJEO or LANTUS once daily for 26 weeks as part of a regimen of combination therapy with noninsulin antidiabetic drugs. At the time of randomization, 808 patients were treated with basal insulin for more than 6 months (Study D) and 862 patients were insulin-naive (Study E).

In Study D, the average age was 58.2 years. The majority of patients were White (94%) and 46% were male; 33% of patients had GFR >90 mL/min/1.73 m^2. The mean BMI was approximately 34.8 kg/m^2. At week 26, treatment with TOUJEO provided a mean reduction in HbA1c that met the prespecified noninferiority margin of 0.4% compared to LANTUS (Table 6). Patients treated with TOUJEO used 12% more basal insulin than patients treated with LANTUS. There were no clinically important differences in body weight between treatment groups.

In Study E, the average age was 58 years. The majority of patients were White (78%) and 58% were male; 29% of patients had GFR >90 mL/min/1.73 m^2. The mean BMI was approximately 33 kg/m^2. At week 26, treatment with TOUJEO provided a mean reduction in HbA1c that met the prespecified noninferiority margin compared to LANTUS (Table 6). Patients treated with TOUJEO used 15% more basal insulin than patients treated with LANTUS. There were no clinically important differences in body weight between treatment groups.

Table 6: Type 2 Diabetes Mellitus – Adult
 | Study C |  | Study D |  | Study E
Treatment duration | 26 weeks |  | 26 weeks |  | 26 weeks
Treatment in combination with | Mealtime insulin analog ± metformin |  | Noninsulin antidiabetic drugs
 | TOUJEO | LANTUS | TOUJEO | LANTUS | TOUJEO | LANTUS
Number of patients treated [m-ITT population: Modified intention-to-treat population.] | 404 | 400 | 403 | 405 | 432 | 430
HbA1c (%)
Baseline mean | 8.13 | 8.14 | 8.27 | 8.22 | 8.49 | 8.58
Adjusted mean change from baseline | -0.90 | -0.87 | -0.73 | -0.70 | -1.42 | -1.46
Adjusted mean difference [Treatment difference: TOUJEO – LANTUS.] | -0.03 |  | -0.03 |  | 0.04
[95% Confidence interval] | [-0.14 to 0.08] |  | [-0.17 to 0.10] |  | [-0.09 to 0.17]
Fasting Plasma Glucose (mg/dL)
Baseline mean | 157 | 160 | 149 | 142 | 179 | 184
Adjusted mean change from baseline | -29 | -30 | -18 | -22 | -61 | -68
Adjusted mean difference | 0.8 |  | 3 |  | 7
[95% Confidence interval] | [-5 to 7] |  | [-3 to 9] |  | [2 to 12]

Safety Outcomes Trial

No clinical studies to establish the cardiovascular safety of TOUJEO have been conducted. A cardiovascular outcomes trial, ORIGIN, has been conducted with LANTUS. It is unknown whether the results of ORIGIN can be applied to TOUJEO.

The Outcome Reduction with Initial Glargine Intervention trial (i.e., ORIGIN) was an open-label, randomized, 12,537 patient study that compared LANTUS to standard care on the time to first occurrence of a major adverse cardiovascular event (MACE). MACE was defined as the composite of CV death, nonfatal myocardial infarction, and nonfatal stroke. The incidence of MACE was similar between LANTUS and standard care in ORIGIN (Hazard Ratio [95% CI] for MACE; 1.02 [0.94, 1.11]).

In the ORIGIN trial, the overall incidence of cancer (all types combined) (Hazard Ratio [95% CI]; 0.99 [0.88, 1.11]) or death from cancer (Hazard Ratio [95% CI]; 0.94 [0.77, 1.15]) was also similar between treatment groups.

16 HOW SUPPLIED/STORAGE AND HANDLING

16.1 How Supplied

TOUJEO (insulin glargine) injection, 300 units/mL (U-300), is a clear and colorless solution and is available as:

TOUJEO | Total volume | Total units available in presentation | Max dose per injection | Dose increment | NDC number | Package size
SoloStar single-patient-use prefilled pen | 1.5 mL | 450 units | 80 units | 1 unit | 0024-5869-03 | 3 pens/pack
Max SoloStar single-patient-use prefilled pen | 3 mL | 900 units | 160 units | 2 units | 0024-5871-02 | 2 pens/pack

Needles are not included in the packs of TOUJEO SoloStar or TOUJEO Max SoloStar single-patient-use prefilled pen.

BD (such as BD Ultra-Fine®), Ypsomed (such as Clickfine®) or Owen Mumford (such as Unifine® Pentips®) needles‡ can be used in conjunction with TOUJEO SoloStar or TOUJEO Max SoloStar single-patient-use prefilled pen and are sold separately.

A new sterile needle must be attached before each injection. TOUJEO SoloStar or TOUJEO Max SoloStar single-patient-use prefilled pens must never be shared between patients, even if the needle is changed.

16.2 Storage

Dispense in the original sealed carton with the enclosed Instructions for Use.

TOUJEO SoloStar or TOUJEO Max SoloStar prefilled pen should not be stored in the freezer and should not be allowed to freeze. Discard TOUJEO prefilled pen if it has been frozen. Protect TOUJEO SoloStar/TOUJEO Max SoloStar from direct heat and light.

Storage conditions are summarized in the following table:

TOUJEO | Not in-use (unopened) Refrigerated 36°F–46°F (2°C–8°C) | In-use (opened) [To prevent degradation, always store the prefilled pens with the cap on during in-use period.] Room temperature only (Do not refrigerate) up to 86°F (30°C)
1.5 mL SoloStar single-patient-use prefilled pen | Until expiration date | 56 days
3 mL Max SoloStar single-patient-use prefilled pen | Until expiration date | 56 days

17 PATIENT COUNSELING INFORMATION

Advise the patient to read the FDA-approved patient labeling (Patient Information and Instructions for Use). There are separate Instructions for Use for TOUJEO SoloStar and TOUJEO Max SoloStar.

Never Share a TOUJEO SoloStar or TOUJEO Max SoloStar Pen Between Patients

Advise patients that they must never share TOUJEO SoloStar or TOUJEO Max SoloStar pen with another person even if the needle is changed. Pen sharing poses a risk for transmission of blood-borne pathogens [see Warnings and Precautions (5.1)].

Hyperglycemia or Hypoglycemia

Inform patients that hypoglycemia is the most common adverse reaction with insulin. Inform patients of the symptoms of hypoglycemia (e.g., impaired ability to concentrate and react). This may present a risk in situations where these abilities are especially important, such as driving or operating other machinery. Advise patients who have frequent hypoglycemia or reduced or absent warning signs of hypoglycemia to use caution when driving or operating machinery [see Warnings and Precautions (5.2, 5.3)].

Advise patients that changes in insulin regimen can predispose to hyperglycemia or hypoglycemia and that changes in insulin regimen should be made under close medical supervision [see Warnings and Precautions (5.2)].

Inform patients that if they change to TOUJEO from other basal insulins they may experience higher average fasting plasma glucose levels in the first weeks of therapy. Advise patients to monitor glucose daily when initiating TOUJEO [see Warnings and Precautions (5.2)].

Hypoglycemia Due to Medication Errors

Instruct patients to always check the insulin label before each injection [see Warnings and Precautions (5.4)]. The "300 units/mL (U-300)" is highlighted in honey gold on the labels of TOUJEO and TOUJEO Max SoloStar single-patient-use prefilled pens.

Inform patients that TOUJEO contains 300 units of insulin glargine per mL (U-300) compared to formulations of insulin glargine that contain 100 units/mL (U-100). To avoid dosing errors and potential overdose, instruct patients to never use a syringe to remove TOUJEO from the TOUJEO SoloStar or TOUJEO Max SoloStar single-patient-use prefilled pen [see Warnings and Precautions (5.4)].

Inform patients that the dose counter of TOUJEO SoloStar or TOUJEO Max SoloStar single-patient-use prefilled pen shows the number of units of TOUJEO to be injected and no dose recalculation is required [see Dosage and Administration (2.1, 2.4)].

Hypersensitivity Reactions

Advise patients that hypersensitivity reactions have occurred with TOUJEO. Inform patients on the symptoms of hypersensitivity reactions [see Warnings and Precautions (5.5)].

Manufactured by:
sanofi-aventis U.S. LLC
Morristown, NJ 07960
A SANOFI COMPANY
U.S. License No. 1752

For patent information: https://www.sanofi.us/en/products-and-resources/patents

©2025 sanofi-aventis U.S. LLC

LANTUS, TOUJEO, SoloStar, and TOUJEO Max SoloStar are registered trademarks of sanofi-aventis U.S. LLC.

‡Other brands listed are the registered trademarks of their respective owners and are not trademarks of sanofi-aventis U.S. LLC.

Patient Information
TOUJEO® U-300 [too-JAY-oh]
(insulin glargine)
injection, for subcutaneous use
300 units/mL (U-300)

Do not share your TOUJEO SoloStar® or TOUJEO Max SoloStar® pen with other people, even if the needle has been changed. You may give other people a serious infection, or get a serious infection from them.

What is TOUJEO?

- TOUJEO is a long-acting man-made insulin used to control high blood sugar in adults and children who are 6 years of age and older with diabetes mellitus.
- TOUJEO is not for the treatment of diabetic ketoacidosis.
- It is not known if TOUJEO is safe and effective in children under 6 years of age.

Who should not use TOUJEO?

Do not use TOUJEO if you:

- are having an episode of low blood sugar (hypoglycemia).
- have an allergy to insulin glargine or any of the ingredients in TOUJEO. See the end of this Patient Information leaflet for a complete list of ingredients in TOUJEO.

What should I tell my healthcare provider before using TOUJEO?

Before using TOUJEO, tell your healthcare provider about all your medical conditions, including if you:

- have liver or kidney problems.
- take other medicines, especially ones called TZDs (thiazolidinediones).
- have heart failure or other heart problems. If you have heart failure, it may get worse while you take TZDs with TOUJEO.
- are pregnant, planning to become pregnant, or are breastfeeding. It is not known if TOUJEO may harm your unborn or breastfeeding baby.

Tell your healthcare provider about all the medicines you take, including prescription and over-the-counter medicines, vitamins, and herbal supplements.

Before you start using TOUJEO, talk to your healthcare provider about low blood sugar and how to manage it.

How should I use TOUJEO?

- TOUJEO is available in 2 single-patient-use prefilled pens: TOUJEO SoloStar and TOUJEO Max SoloStar. Your healthcare provider will tell you which TOUJEO pen is right for you.
- Read the detailed Instructions for Use that come with your TOUJEO SoloStar or TOUJEO Max SoloStar single-patient-use prefilled pen.
- Use TOUJEO exactly as your healthcare provider tells you to. Your healthcare provider should tell you how much TOUJEO to use and when to use it.
- Know the amount of TOUJEO you use. Do not change the amount of TOUJEO you use unless your healthcare provider tells you to.
- Check your insulin label each time you give your injection to make sure you are using the correct insulin.
- Do not use a syringe to remove TOUJEO from your TOUJEO SoloStar or TOUJEO Max SoloStar single-patient-use prefilled pen. This can cause you to give yourself too much insulin. TOUJEO has 3 times as much insulin (300 units/mL) in 1 mL as compared to other insulin glargine products (U-100 units/mL) pens.
- Do not re-use needles. Always use a new needle for each injection. Reusing needles increases your chance of having blocked needles, which can cause you to get the wrong dose of TOUJEO. Using a new needle for each injection also lowers your risk of getting an infection. If your needle is blocked, follow the instructions in Step 3 of the Instructions for Use.
- TOUJEO should be used 1 time each day and at the same time each day.
- TOUJEO is injected under the skin (subcutaneously) of your upper legs (thighs), upper arms, or stomach area (abdomen).
- Do not use TOUJEO in an insulin pump or inject TOUJEO into your vein (intravenously).
- Change (rotate) your injection sites within the area you choose with each dose to reduce your risk of getting pits or thickening of the skin (lipodystrophy) and lumps in the skin (localized cutaneous amyloidosis) at the injection sites.
  - Do not use the exact same spot for each injection.
  - Do not inject where the skin has pits, is thickened, or has lumps.
  - Do not inject where the skin is tender, bruised, scaly or hard, or into scars or damaged skin.
- Do not mix TOUJEO with any other type of insulin or liquid medicine.
- Check your blood sugar levels. Ask your healthcare provider what your blood sugar should be and when you should check your blood sugar levels.

Keep TOUJEO and all medicines out of the reach of children.

Your dose of TOUJEO may need to change because of:

- a change in level of physical activity or exercise, weight gain or loss, increased stress, illness, change in diet, or because of other medicines you take.

What should I avoid while using TOUJEO?

While using TOUJEO do not:

- drive or operate heavy machinery, until you know how TOUJEO affects you.
- drink alcohol or use over-the-counter medicines that contain alcohol.

What are the possible side effects of TOUJEO?

TOUJEO may cause serious side effects that can lead to death, including:

- low blood sugar (hypoglycemia). Signs and symptoms that may indicate low blood sugar include:
  - dizziness or light-headedness, sweating, confusion, headache, blurred vision, slurred speech, shakiness, fast heartbeat, anxiety, irritability or mood change, and hunger.
- severe allergic reaction (whole body reaction). Get medical help right away if you have any of these signs or symptoms of a severe allergic reaction:
  - a rash over your whole body, trouble breathing, a fast heartbeat, or sweating.
- low potassium in your blood (hypokalemia).
- heart failure. Taking certain diabetes pills called TZDs (thiazolidinediones) with TOUJEO may cause heart failure in some people. This can happen even if you have never had heart failure or heart problems before. If you already have heart failure it may get worse while you take TZDs with TOUJEO. Your healthcare provider should monitor you closely while you are taking TZDs with TOUJEO. Tell your healthcare provider if you have any new or worse symptoms of heart failure including:
  - shortness of breath, swelling of your ankles or feet, sudden weight gain.
  Treatment with TZDs and TOUJEO may need to be changed or stopped by your healthcare provider if you have new or worse heart failure.

Get emergency medical help if you have:

- trouble breathing, shortness of breath, fast heartbeat, swelling of your face, tongue, or throat, sweating, extreme drowsiness, dizziness, confusion.

The most common side effects of TOUJEO include:

- low blood sugar (hypoglycemia), weight gain, itching, rash, swelling, allergic reactions, including reactions at your injection site, skin thickening or pits at the injection site (lipodystrophy).

These are not all the possible side effects of TOUJEO. Call your doctor for medical advice about side effects. You may report side effects to FDA at 1-800-FDA-1088.

General information about the safe and effective use of TOUJEO.

Medicines are sometimes prescribed for purposes other than those listed in a Patient Information leaflet. Do not use TOUJEO for a condition for which it was not prescribed. Do not give TOUJEO to other people, even if they have the same symptoms that you have. It may harm them.

This Patient Information leaflet summarizes the most important information about TOUJEO. If you would like more information, talk with your healthcare provider. You can ask your pharmacist or healthcare provider for information about TOUJEO that is written for health professionals.

What are the ingredients in TOUJEO?

- Active ingredient: insulin glargine
- Inactive ingredients: glycerin, metacresol, zinc and Water for Injection, USP. Hydrochloric acid and sodium hydroxide may be added to adjust the pH.

Manufactured by: sanofi-aventis U.S. LLC, Morristown, NJ 07960, A SANOFI COMPANY.
U.S. License No. 1752
For more information, go to www.TOUJEO.com or call 1-800-633-1610.

This Patient Information has been approved by the U.S. Food and Drug Administration
Revised: May 2025

Instructions for Use

TOUJEO® U-300 SoloStar® [too-JAY-oh]
(insulin glargine)
injection, for subcutaneous use
300 units/mL (U-300)
1.5 mL single-patient-use prefilled pen

Read this first

Do not share your TOUJEO SoloStar pen with other people, even if the needle has been changed. You may give other people a serious infection, or get a serious infection from them.

TOUJEO contains 300 units/mL of insulin glargine

- Do not re-use needles. If you do, you might not get your dose (underdosing) or get too much (overdosing) as the needle could block.
- Do not use a syringe to remove insulin from your pen. If you do, you will get too much insulin. The scale on most syringes is made for U-100 (non-concentrated) insulin only.
- The dose selector of your TOUJEO SoloStar pen dials by 1 unit.

People who are blind or have vision problems should not use the TOUJEO SoloStar pen without help from a person trained to use the TOUJEO SoloStar pen.

Important information

- Do not use your pen if it is damaged or if you are not sure that it is working properly.
- Always perform a safety test (see Step 3).
- Always carry a spare pen and spare needles in case they are lost or stop working.
- Change (rotate) your injection sites within the area you choose for each dose (see "Places to inject").

Learn to inject

- Talk with your healthcare provider about how to inject, before using your pen.
- Read all of these instructions before using your pen. If you do not follow all of these instructions, you may get too much or too little insulin.

Need help?

If you have any questions about your pen or about diabetes, ask your healthcare provider, go to www.Toujeo.com or call sanofi-aventis at 1-800-633-1610.

Extra items you will need:

- a new sterile needle (not included with the pen) (see Step 2).
- an alcohol swab.
- a puncture-resistant container for used needles and pens (see "Throwing your pen away").

Places to inject

- Inject your insulin exactly as your healthcare provider has shown you.
- Inject your insulin under the skin (subcutaneously) of your upper legs (thighs), upper arms, or stomach area (abdomen).
- Change (rotate) your injection sites within the area you choose for each dose to reduce your risk of getting pits or thickening of the skin (lipodystrophy) and lumps in the skin (localized cutaneous amyloidosis) at the injection sites.
- Do not inject where the skin has pits, is thickened, or has lumps.
  - Do not inject where the skin is tender, bruised, scaly or hard, or into scars or damaged skin.

Get to know your pen

Step 1: Check your pen

Take a new pen out of the refrigerator at least 1 hour before you inject. Cold insulin is more painful to inject.

1A Check the name and expiration date on the label of your pen.
  - Make sure you have the correct insulin.
  - Do not use your pen after the expiration date printed on the label.
1B Pull off the pen cap.
1C Check that the insulin is clear.
  - Do not use the pen if the insulin looks cloudy, colored or contains particles.
1D Wipe the rubber seal with an alcohol swab.

If you have other injector pens

- Making sure you have the correct medicine is especially important if you have other injector pens.

Step 2: Attach a new needle

- Do not re-use needles. Always use a new sterile needle for each injection. This helps stop blocked needles, contamination and infection.
- Always use needles* from BD (such as BD Ultra-Fine®), Ypsomed (such as Clickfine®), or Owen Mumford (such as Unifine® Pentips®).

2A Take a new needle and peel off the protective seal.
2B Keep the needle straight and screw it onto the pen until fixed. Do not over-tighten.
2C Pull off the outer needle cap. Keep this for later.
2D Pull off the inner needle cap and throw away.

Handling needles

- Be careful when you are handling needles to help prevent accidental needle-stick injury. You may give other people a serious infection, or get a serious infection from them.

Step 3: Do a safety test

Always do a safety test before each injection to:

- check your pen and the needle to make sure they are working properly.
- make sure that you get the correct insulin dose.

If the pen is new, you must perform safety tests before you use the pen for the first time until you see insulin coming out of the needle tip. If you see insulin coming out of the needle tip, the pen is ready to use. If you do not see insulin coming out before taking your dose, you could get an underdose or no insulin at all. This could cause high blood sugar.

3A Select 3 units by turning the dose selector until the dose pointer is at the mark between 2 and 4.
3B Press the injection button all the way in.
  - When insulin comes out of the needle tip, your pen is working correctly.

If no insulin appears:

- You may need to repeat this step up to 3 times before seeing insulin.
- If no insulin comes out after the third time, the needle may be blocked. If this happens:
  - change the needle (see Step 6 and Step 2),
  - then repeat the safety test (see Step 3).
- Do not use your pen if there is still no insulin coming out of the needle tip. Use a new pen.
- Do not use a syringe to remove insulin from your pen.

If you see air bubbles

- You may see air bubbles in the insulin. This is normal, they will not harm you.

Step 4: Select the dose

- Do not select a dose or press the injection button without a needle attached. This may damage your pen.
- TOUJEO, SoloStar is made to deliver the number of insulin units that your healthcare provider prescribed. You do not need to do any dose calculations.
- The dose selector of your TOUJEO SoloStar pen dials by 1 unit.

4A Make sure a needle is attached and the dose is set to "0."
4B Turn the dose selector until the dose pointer lines up with your dose.
  - Set the dose by turning the dose selector to a line in the dose window. Each line equals 1 unit.
  - The dose selector clicks as you turn it.
  - Always check the number in the dose window to make sure you dialed the correct dose.
  - Do not dial your dose by counting the clicks. You may dial the wrong dose. This may lead to you getting too much insulin or not enough insulin.
  - If you turn past your dose, you can turn back down.
  - If there are not enough units left in your pen for your dose, the dose selector will stop at the number of units left.
  - If you cannot select your full prescribed dose, split the dose into 2 injections or use a new pen. If you use a new pen, perform a safety test (see Step 3).

How to read the dose window

The dose selector dials by 1 unit.

Even numbers are shown in line with the dose pointer:

30 units selected

Odd numbers are shown as a line between even numbers:

29 units selected

Units of insulin in your pen

- Your pen contains a total of 450 units of insulin. You can select doses from 1 to 80 units. Each pen contains more than 1 dose.
- You can see roughly how many units of insulin are left by looking at where the plunger is on the insulin scale.

Step 5: Inject your dose

If you find it hard to press the injection button in, do not force it as this may break your pen. See the section below for help.

5A Choose a place to inject as shown in the picture labeled "Places to inject."
  - The site you choose for the injection should be clean and dry.
  - If your skin is dirty, clean it as instructed by your healthcare provider.
5B Push the needle into your skin as shown by your healthcare provider.
  - Do not touch the injection button yet.
5C Place your thumb on the injection button. Then press all the way in and hold.
  - Do not press at an angle. Your thumb could block the dose selector from turning.
5D Keep the injection button held in and when you see "0" in the dose window, slowly count to 5.
  - This will make sure you get your full dose.
5E After holding and slowly counting to 5, release the injection button. Then remove the needle from your skin.

If you find it hard to press the injection button in:

- Change the needle (see Step 6 and Step 2) then do a safety test (see Step 3).
- If you still find it hard to press in, get a new pen.
- Do not use a syringe to remove insulin from your pen.

Step 6: Remove the needle

- Take care when handling needles to prevent needle injury and cross-infection.
- Do not put the inner needle cap back on.

6A Grip the widest part of the outer needle cap. Keep the needle straight and guide it into the outer needle cap.
  Then push firmly on.
  - The needle can puncture the cap if it is recapped at an angle.
6B Grip and squeeze the widest part of the outer needle cap. Turn your pen several times with your other hand to remove the needle.
  - Try again if the needle does not come off the first time.
6C Throw away the used needle in a puncture-resistant container (see "Throwing your pen away" at the end of this Instructions for Use).
6D Put the pen cap back on.
  - Do not put the pen back in the refrigerator.

Use by

- Only use your pen for up to 56 days after its first use.

How to store your pen

Before first use

- Keep new pens in the refrigerator between 36°F and 46°F (2°C and 8°C).
- Do not freeze. Throw away your pen if it has been frozen (See "Throwing your pen away").

After first use

- Keep your pen at room temperature up to 86°F (30°C).
- Protect your pen from direct heat and light.
- Do not put your pen back in the refrigerator.
- Do not store your pen with the needle attached.
- Store your pen with the pen cap on.
- Keep TOUJEO SoloStar pens and needles out of the reach of children.

How to care for your pen

Handle your pen with care

- Do not drop your pen or knock it against hard surfaces.
- If you think that your pen may be damaged, do not try to fix it. Use a new one.

Protect your pen from dust and dirt

- You can clean the outside of your pen by wiping it with a damp cloth (water only). Do not soak, wash or lubricate your pen. This may damage it.

Throwing your pen away

- The used TOUJEO SoloStar pen may be thrown away in your household trash after you have removed the needle.
- Put the used needle in a FDA-cleared sharps disposal container right away after use.
  Do not throw away (dispose of) needles in your household trash.
- If you do not have a FDA-cleared sharps disposal container, you may use a household container that is:
  - made of a heavy-duty plastic,
  - can be closed with a tight-fitting, puncture-resistant lid, without sharps being able to come out,
  - upright and stable during use,
  - leak-resistant, and
  - properly labeled to warn of hazardous waste inside the container.
- When your sharps disposal container is almost full, you will need to follow your community guidelines for the right way to dispose of your sharps disposal container. There may be state or local laws about how you should throw away used needles and syringes. For more information about safe sharps disposal, and for specific information about sharps disposal in the state that you live in, go to the FDA's website at: http://www.fda.gov/safesharpsdisposal.
- Do not dispose of your used sharps disposal container in your household trash unless your community guidelines permit this. Do not recycle your used sharps disposal container.

Manufactured by:
sanofi-aventis U.S. LLC
Morristown, NJ 07960
A SANOFI COMPANY
U.S. License No. 1752

©2025 sanofi-aventis U.S. LLC

TOUJEO and SoloStar are registered trademarks of sanofi-aventis U.S. LLC.

Other brands listed are the registered trademarks of their respective owners and are not trademarks of sanofi-aventis U.S. LLC.

This Instructions for Use has been approved by the U.S. Food and Drug Administration.

Revised: May 2025

Instructions for Use

TOUJEO U-300 Max SoloStar® [too-JAY-oh]
(insulin glargine)
injection, for subcutaneous use
300 units/mL (U-300)
3 mL single-patient-use prefilled pen

Read this first

Do not share your TOUJEO Max SoloStar pen with other people, even if the needle has been changed. You may give other people a serious infection, or get a serious infection from them.

TOUJEO contains 300 units/mL of insulin glargine

- Do not re-use needles. If you do, you might not get your dose (underdosing) or get too much (overdosing) as the needle could block.
- Do not use a syringe to remove insulin from your pen. If you do, you will get too much insulin. The scale on most syringes is made for U-100 (non-concentrated) insulin only.
- The dose selector of your TOUJEO Max SoloStar pen dials by 2 units.

People who are blind or have vision problems should not use the TOUJEO Max SoloStar pen without help from a person trained to use the TOUJEO Max SoloStar pen.

Important information

- Do not use your pen if it is damaged or if you are not sure that it is working properly.
- Always perform a safety test (see Step 3).
- Always carry a spare pen and spare needles in case they are lost or stop working.
- Change (rotate) your injection sites within the area you choose for each dose (see "Places to inject").

Learn to inject

- Talk with your healthcare provider about how to inject, before using your pen.
- Read all of these instructions before using your pen. If you do not follow all of these instructions, you may get too much or too little insulin.

Need help?

If you have any questions about your pen or about diabetes, ask your healthcare provider, go to www.Toujeo.com or call sanofi-aventis at 1-800-633-1610.

Extra items you will need:

- a new sterile needle (not included with the pen) (see Step 2).
- an alcohol swab.
- a puncture-resistant container for used needles and pens (see "Throwing your pen away").

Places to inject

- Inject your insulin exactly as your healthcare provider has shown you.
- Inject your insulin under the skin (subcutaneously) of your upper legs (thighs), upper arms, or stomach area (abdomen).
- Change (rotate) your injection sites within the area you choose for each dose to reduce your risk of getting pits or thickening of the skin (lipodystrophy) and lumps in the skin (localized cutaneous amyloidosis) at the injection sites.
- Do not inject where the skin has pits, is thickened, or has lumps.
  - Do not inject where the skin is tender, bruised, scaly or hard, or into scars or damaged skin.

Get to know your pen

Step 1: Check your pen

Take a new pen out of the refrigerator at least 1 hour before you inject. Cold insulin is more painful to inject.

1A Check the name and expiration date on the label of your pen.
  - Make sure you have the correct insulin.
  - Do not use your pen after the expiration date printed on the label.
1B Pull off the pen cap.
1C Check that the insulin is clear.
  - Do not use the pen if the insulin looks cloudy, colored or contains particles.
1D Wipe the rubber seal with an alcohol swab.

If you have other injector pens

- Making sure you have the correct medicine is especially important if you have other injector pens.

Step 2: Attach a new needle

- Do not re-use needles. Always use a new sterile needle for each injection. This helps stop blocked needles, contamination and infection.
- Always use needles* from BD (such as BD Ultra-Fine®), Ypsomed (such as Clickfine®), or Owen Mumford (such as Unifine® Pentips®) that are 8 mm long or shorter.

2A Take a new needle and peel off the protective seal.
2B Keep the needle straight and screw it onto the pen until fixed. Do not over-tighten.
2C Pull off the outer needle cap. Keep this for later.
2D Pull off the inner needle cap and throw away.

Handling needles

- Be careful when you are handling needles to help prevent accidental needle-stick injury. You may give other people a serious infection, or get a serious infection from them.

Step 3: Do a safety test

Always do a safety test before each injection to:

- check your pen and the needle to make sure they are working properly.
- make sure that you get the correct insulin dose.

If the pen is new, you must perform safety tests before you use the pen for the first time until you see insulin coming out of the needle tip. If you see insulin coming out of the needle tip, the pen is ready to use. If you do not see insulin coming out before taking your dose, you could get an underdose or no insulin at all. This could cause high blood sugar.

3A Select 4 units by turning the dose selector until the dose pointer is at the 4 mark.
3B Press the injection button all the way in.
  - When insulin comes out of the needle tip, your pen is working correctly.

If no insulin appears:

- You may need to repeat this step up to 6 times before seeing insulin.
- If no insulin comes out after the sixth time, the needle may be blocked. If this happens:
  - change the needle (see Step 6 and Step 2),
  - then repeat the safety test (see Step 3).
- Do not use your pen if there is still no insulin coming out of the needle tip. Use a new pen.
- Do not use a syringe to remove insulin from your pen.

If you see air bubbles

- You may see air bubbles in the insulin. This is normal, they will not harm you.

Step 4: Select the dose

- Do not select a dose or press the injection button without a needle attached. This may damage your pen.
- TOUJEO Max SoloStar is made to deliver the number of insulin units that your healthcare provider prescribed. You do not need to do any dose calculations.
- The dose selector of your TOUJEO Max SoloStar pen dials by 2 units and can only dial even doses of insulin.

4A Make sure a needle is attached and the dose is set to "0."
4B Turn the dose selector until the dose pointer lines up with your dose.
  - Set the dose by turning the dose selector to a line in the dose window. Each line equals 2 units.
  - The dose selector clicks as you turn it.
  - Always check the number in the dose window to make sure you dialed the correct dose.
  - Do not dial your dose by counting the clicks. You may dial the wrong dose. This may lead to you getting too much insulin or not enough insulin.
  - If you turn past your dose, you can turn back down.
  - If there are not enough units left in your pen for your dose, the dose selector will stop at the number of units left.
  - If you cannot select your full prescribed dose, split the dose into 2 injections or use a new pen. If you use a new pen, perform a safety test (see Step 3).

How to read the dose window

The dose selector dials by 2 units.

Each line in the dose window is an even number.

60 units selected

58 units selected

Units of insulin in your pen

- Your pen contains a total of 900 units of insulin. You can select doses from 2 to 160 units. The dose is adjusted by 2 units at a time. Each pen contains more than 1 dose.
- You can see roughly how many units of insulin are left by looking at where the plunger is on the insulin scale.

Step 5: Inject your dose

If you find it hard to press the injection button in, do not force it as this may break your pen. See the section below for help.

5A Choose a place to inject as shown in the picture labeled "Places to inject."
  - The site you choose for the injection should be clean and dry.
  - If your skin is dirty, clean it as instructed by your healthcare provider.
5B Push the needle into your skin as shown by your healthcare provider.
  - Do not touch the injection button yet.
5C Place your thumb on the injection button. Then press all the way in and hold.
  - Do not press at an angle. Your thumb could block the dose selector from turning.
5D Keep the injection button held in and when you see "0" in the dose window, slowly count to 5.
  - This will make sure you get your full dose.
5E After holding and slowly counting to 5, release the injection button. Then remove the needle from your skin.

If you find it hard to press the injection button in:

- Change the needle (see Step 6 and Step 2) then do a safety test (see Step 3).
- If you still find it hard to press in, get a new pen.
- Do not use a syringe to remove insulin from your pen.

Step 6: Remove the needle

- Take care when handling needles to prevent needle injury and cross-infection.
- Do not put the inner needle cap back on.

6A Grip the widest part of the outer needle cap. Keep the needle straight and guide it into the outer needle cap.
  Then push firmly on.
  - The needle can puncture the cap if it is recapped at an angle.
6B Grip and squeeze the widest part of the outer needle cap. Turn your pen several times with your other hand to remove the needle.
  - Try again if the needle does not come off the first time.
6C Throw away the used needle in a puncture-resistant container (see "Throwing your pen away" at the end of this Instructions for Use).
6D Put the pen cap back on.
  - Do not put the pen back in the refrigerator.

Use by

- Only use your pen for up to 56 days after its first use.

How to store your pen

Before first use

- Keep new pens in the refrigerator between 36°F and 46°F (2°C and 8°C).
- Do not freeze. Throw away your pen if it has been frozen (see "Throwing your pen away").

After first use

- Keep your pen at room temperature up to 86°F (30°C).
- Protect your pen from direct heat and light.
- Do not put your pen back in the refrigerator.
- Do not store your pen with the needle attached.
- Store your pen with the pen cap on.
- Keep TOUJEO Max SoloStar pens and needles out of the reach of children.

How to care for your pen

Handle your pen with care

- Do not drop your pen or knock it against hard surfaces.
- If you think that your pen may be damaged, do not try to fix it. Use a new one.

Protect your pen from dust and dirt

- You can clean the outside of your pen by wiping it with a damp cloth (water only). Do not soak, wash or lubricate your pen. This may damage it.

Throwing your pen away

- The used TOUJEO Max SoloStar pen may be thrown away in your household trash after you have removed the needle.
- Put the used needle in a FDA-cleared sharps disposal container right away after use. Do not throw away (dispose of) needles in your household trash.
- If you do not have a FDA-cleared sharps disposal container, you may use a household container that is:
  - made of a heavy-duty plastic,
  - can be closed with a tight-fitting, puncture-resistant lid, without sharps being able to come out,
  - upright and stable during use,
  - leak-resistant, and
  - properly labeled to warn of hazardous waste inside the container.
- When your sharps disposal container is almost full, you will need to follow your community guidelines for the right way to dispose of your sharps disposal container. There may be state or local laws about how you should throw away used needles and syringes. For more information about safe sharps disposal, and for specific information about sharps disposal in the state that you live in, go to the FDA's website at:
  http://www.fda.gov/safesharpsdisposal.
- Do not dispose of your used sharps disposal container in your household trash unless your community guidelines permit this. Do not recycle your used sharps disposal container.

Manufactured by:
sanofi-aventis U.S. LLC
Morristown, NJ 07960A SANOFI COMPANY
U.S. License No. 1752

©2025 sanofi-aventis U.S. LLC

TOUJEO and TOUJEO Max SoloStar are registered trademarks of sanofi-aventis U.S. LLC.

Other brands listed are the registered trademarks of their respective owners and are not trademarks of sanofi-aventis U.S. LLC.

This Instructions for Use has been approved by the U.S. Food and Drug Administration.

Revised: May 2025

PRINCIPAL DISPLAY PANEL - 1.5 mL Pen Carton

NDC 0024-5869-03
Rx only

Toujeo® SoloStar®
(insulin glargine) injection

For Single Patient Use Only

300 units/mL (U-300)

For subcutaneous use only
Solution for injection in a disposable insulin delivery device
Do not remove insulin with syringe
Always use a new needle – Do not mix with other insulins
Use only if solution is clear and colorless with no particles visible

Use within 56 days after opening
*Needles not included (see back panel)
Three 1.5 mL prefilled pens – Dispense in this sealed carton

sanofi

PRINCIPAL DISPLAY PANEL - 3 mL Pen Carton

NDC 0024-5871-02
Rx only

Toujeo Max SoloStar®
(insulin glargine) injection

For Single Patient Use Only

300 units/mL (U-300)
Adjusts by 2 units

For subcutaneous use only
Solution for injection in a disposable insulin delivery device
Do not remove insulin with syringe
Always use a new needle – Do not mix with other insulins
Use only if solution is clear and colorless with no particles visible

Use within 56 days after opening
*Needles not included (see back panel)
Two 3 mL prefilled pens – Dispense in this sealed carton

sanofi